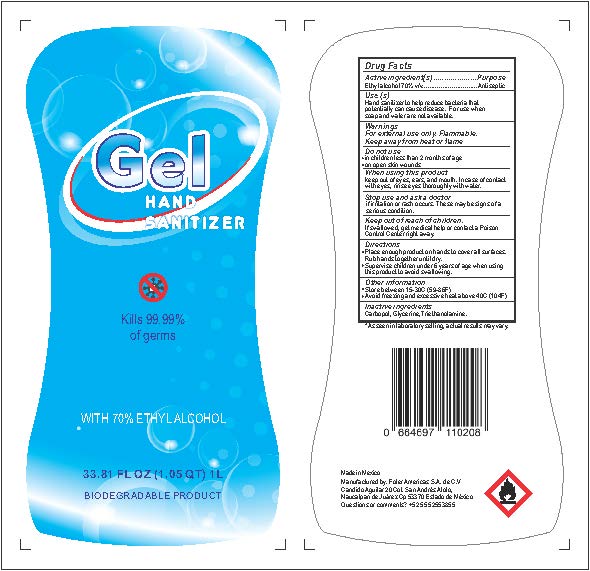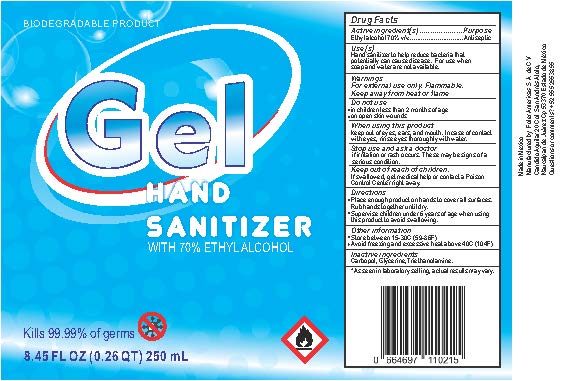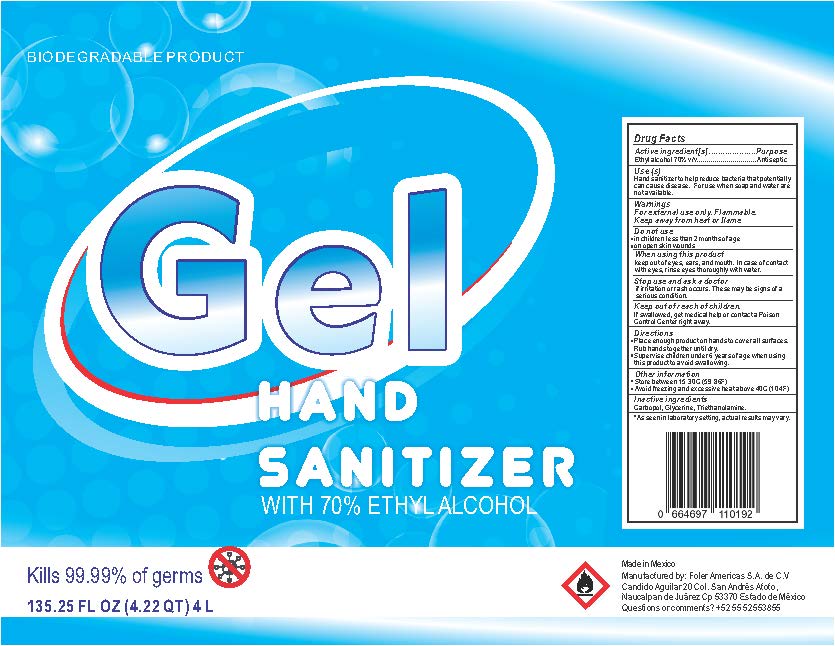 DRUG LABEL: Hand Sanitizer
NDC: 78635-100 | Form: GEL
Manufacturer: Premium Printing Inc.
Category: otc | Type: HUMAN OTC DRUG LABEL
Date: 20200626

ACTIVE INGREDIENTS: ALCOHOL 175 mL/250 mL
INACTIVE INGREDIENTS: POLYACRYLIC ACID (250000 MW); TRIETHANOLAMINE ISOSTEARATE; GLYCERIN

Premium Gel Hand Sanitizer

Active Ingredient

Ethyl Alcohol 70%

Purpose

Antiseptic

Uses

Hand sanitizer to help reduce bacteria that potentially can cause disease. For use when soap and water are not available.

Warnings

For External Use only. Flammable. Keep away from heat or flame.

Do not use

In children less than 2 months of age. On open skin wounds.

When using this product

Keep out of eyes, ears, and mouth. In case of contact with eyes, rinse eyes thoroughly with water.

Stop use and ask a doctor.

If irritation or rash occurs. These may be signs of a serious condition.

Keep out of reach of children.

If swallowed, get medical help or contact a Poison Control Center immediately.

Directions

Place enough product on hands to cover all surfaces. Rub hands together until dry. Supervise children under 6 years of age when using this product to avoid swallowing.

Other Information

Store between 15-30C (59-86F)

Avoid freezing and excessive heat above 40C (104F)

Inactive Ingredients

Carbopol, Glycerin, Triethanolamine